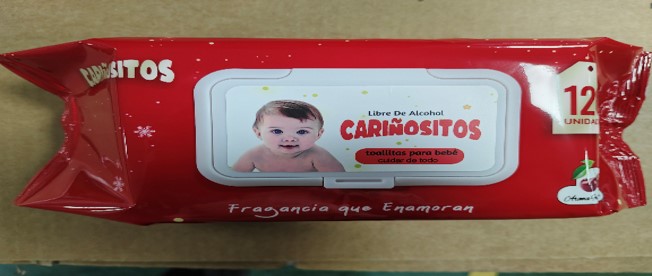 DRUG LABEL: Baby Wipes
NDC: 79539-401 | Form: CLOTH
Manufacturer: Shandong Yayun Sanitary Products Co., Ltd.
Category: otc | Type: HUMAN OTC DRUG LABEL
Date: 20241120

ACTIVE INGREDIENTS: PROPYLENE GLYCOL 1 g/1 1
INACTIVE INGREDIENTS: PHENOXYETHANOL; DISODIUM HEDTA; AQUA; BENZALKONIUM CHLORIDE; CANANGA OIL; SODIUM CITRATE; TEA TREE OIL; .ALPHA.-TOCOPHEROL ACETATE; ALOE VERA LEAF; CETYLPYRIDINIUM CHLORIDE; GLYCERIN

Baby Wipes

Baby Wipes

Purpose

Antiseptic, Baby Wipes

Use

Baby Wipes to help reduce bacteria that potentially can cause disease. For use when soap and water are not available.

Warnings

For external use only. Flammable. Keep away from heat or flame

Do not use

- on open skin wounds

When using this product keep out of eyes, ears, and mouth. In case of contact with eyes, rinse eyes thoroughly with water.
Stop use and ask a doctor if irritation or rash occurs. These may be signs of a serious condition.
Keep out of reach of children. If swallowed, get medical help or contact a Poison Control Center right away.

Stop use and ask a doctor if irritation or rash occurs. These may be signs of a serious condition.

Keep out of reach of children. If swallowed, get medical help or contact a Poison Control Center right away.

Directions

- Wipe the surface of the skin and let it dry naturally
- Supervise children under 6 years of age when using this product to avoid swallowing.

Other information

- Store between 15-30C (59-86F)
- Avoid freezing and excessive heat above 40C (104F)

Inactive ingredients

WATER
Aloe Barbadensis Leaf Extract
Chamomile Extract
Phenoxyethanol
DMDM Hydantoin
Ethylhexylglycerin
Benzalkonium Chloride